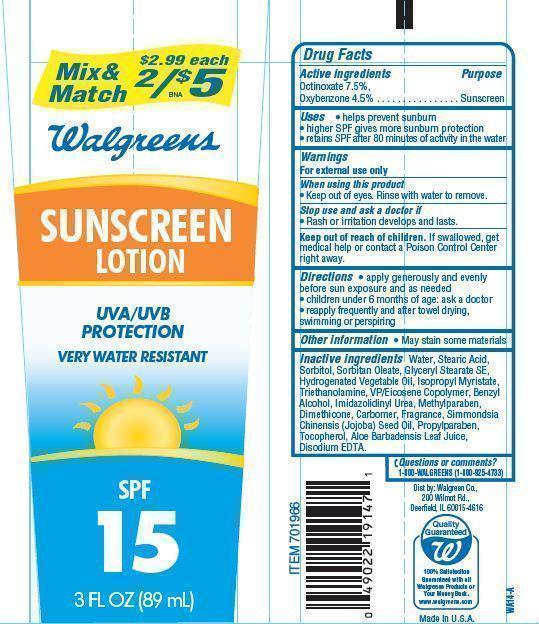 DRUG LABEL: Walgreens Sunscreen
NDC: 0363-4001 | Form: LOTION
Manufacturer: WALGREEN CO.
Category: otc | Type: HUMAN OTC DRUG LABEL
Date: 20121204

ACTIVE INGREDIENTS: OCTINOXATE 7.5 g/100 g; OXYBENZONE  4.5 g/100 g
INACTIVE INGREDIENTS: WATER; STEARIC ACID; SORBITOL; SORBITAN MONOOLEATE; GLYCERYL STEARATE SE; ISOPROPYL MYRISTATE; TROLAMINE; BENZYL ALCOHOL; IMIDUREA; METHYLPARABEN; DIMETHICONE; JOJOBA OIL; PROPYLPARABEN; TOCOPHEROL; ALOE VERA LEAF; EDETATE DISODIUM

Drug Facts

Active Ingredients

Octinoxate 7.5%

Oxybenzone 4.5%

Purpose

Sunscreen

Uses

- helps prevent sunburn
- higher SPF gives more sunburn protection
- retains SPF after 80 minutes of activity in the water

Warnings

For external use only

When using this product

- keep out of eyes. Rinse with water to remove.

Stop use and ask a doctor if

- rash or irritation develops and lasts.

Keep out of the reach of children.

If swallowed get medical help or contact a Poison Control Center right away.

Directions

- apply generously and evenly before sun exposure and as needed
- children under 6 months of age:ask a doctor
- reapply frequently and after towel drying, swimming or perspiring.

Inactive Ingredients

Water, Stearic Acid, Sorbitol, Sorbitan Oleate, Glyceryl Stearate SE, Hydrogenated Vegetable oil Isopropyl Myristate, Triethanolamine,VP/Eicosene Copolymer, Benzyl Alcohol, Imadazolidinyl Urea, Methylparaben, Dimethicone,Carbomer, Fragrance,Simmondsia Chinensis(Jojoba) Seed Oil, Propylparaben, Tocopherol, Aloe Barbadensis Leaf Juice, Disodium EDTA.

Principal Display Panel

Mix and Match $2.99 each
2/$5
Walgreens
SUNSCREEN
LOTION
UVA/UVB
PROTECTION
VERY WATER RESISTANT
SPF
15
3 FL OZ (89 mL)